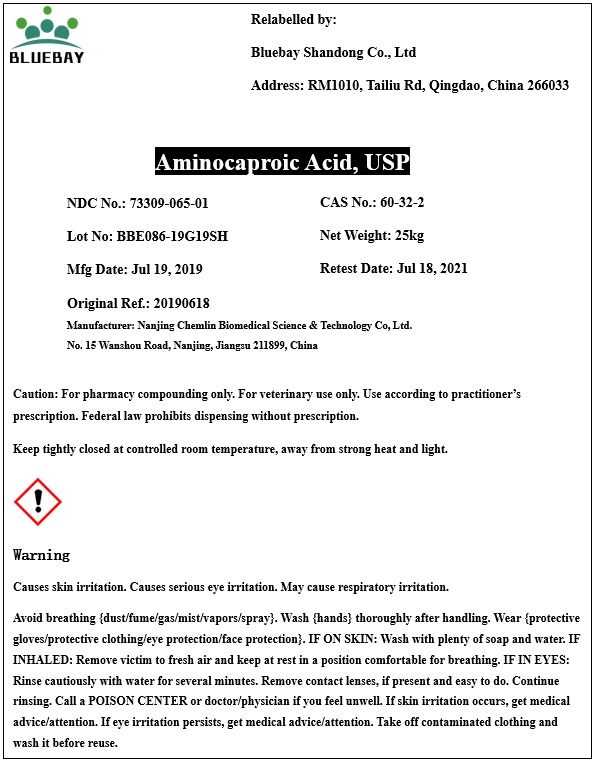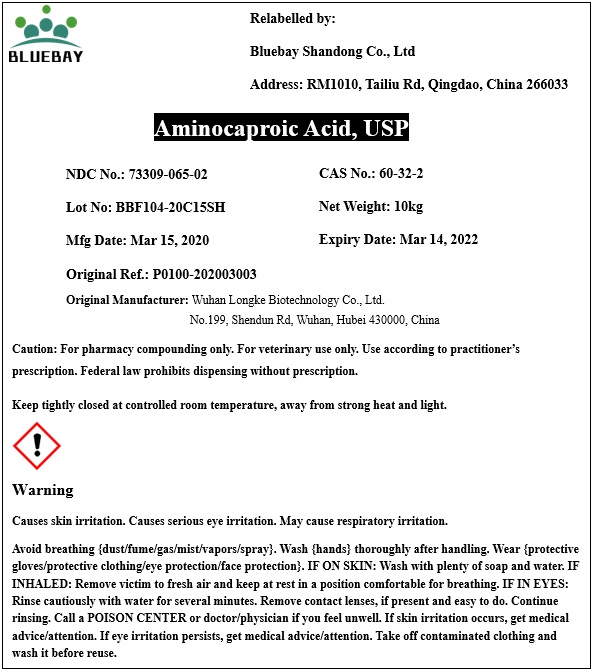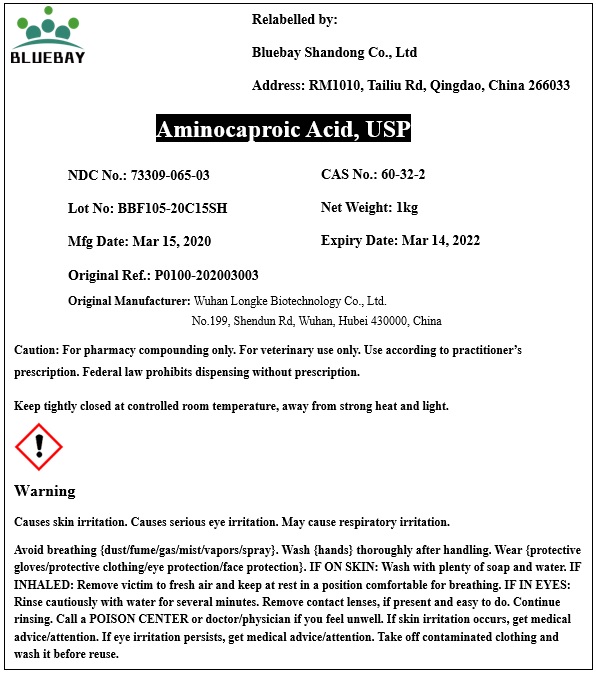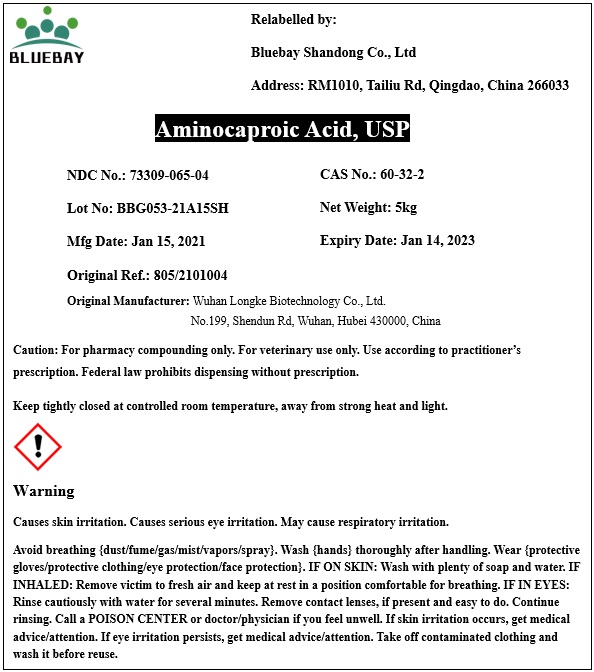 DRUG LABEL: Aminocaproic Acid
NDC: 73309-065 | Form: POWDER
Manufacturer: BLUEBAY SHANDONG CO.,LTD
Category: other | Type: BULK INGREDIENT
Date: 20210219

ACTIVE INGREDIENTS: AMINOCAPROIC ACID 1 kg/1 kg

Aminocaproic Acid